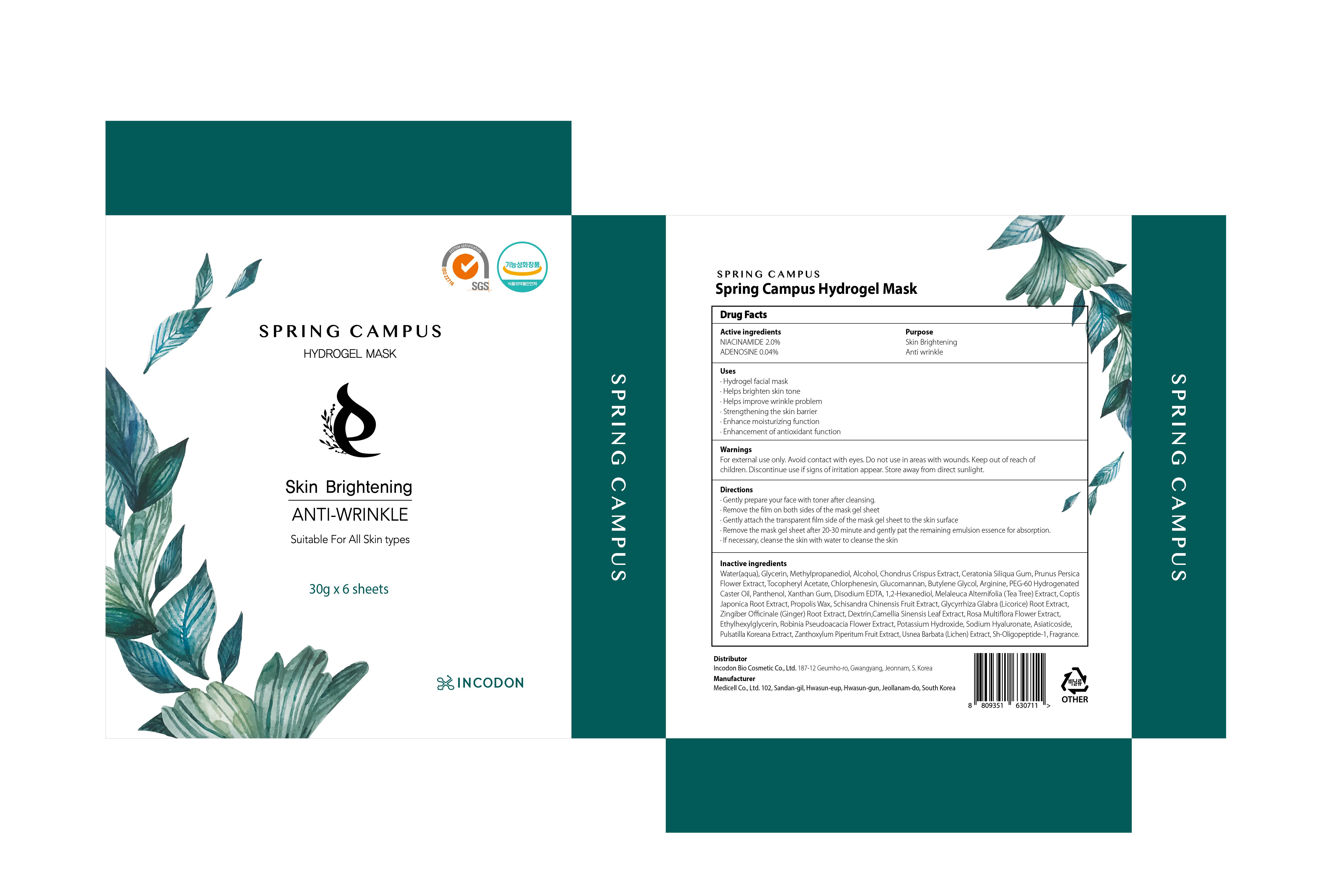 DRUG LABEL: Spring Campus Hydrogel Mask
NDC: 82074-010 | Form: PATCH
Manufacturer: INCODON BIOCOSMETIC Co., Ltd.
Category: otc | Type: HUMAN OTC DRUG LABEL
Date: 20210702

ACTIVE INGREDIENTS: NIACINAMIDE 0.6 g/30 g; ADENOSINE 0.012 g/30 g
INACTIVE INGREDIENTS: Water; Glycerin; Methylpropanediol

ACTIVE INGREDIENTS

NIACINAMIDE 2.0%
ADENOSINE 0.04%

INACTIVE INGREDIENTS

Water(aqua), Glycerin, Methylpropanediol, Alcohol, Chondrus Crispus Extract, Ceratonia Siliqua Gum, Prunus Persica Flower Extract, Tocopheryl Acetate, Chlorphenesin, Glucomannan, Butylene Glycol, Arginine, PEG-60 Hydrogenated Caster Oil, Panthenol, Xanthan Gum, Disodium EDTA, 1,2-Hexanediol, Melaleuca Alternifolia (Tea Tree) Extract, Coptis Japonica Root Extract, Propolis Wax, Schisandra Chinensis Fruit Extract, Glycyrrhiza Glabra (Licorice) Root Extract, Zingiber Officinale (Ginger) Root Extract, Dextrin,Camellia Sinensis Leaf Extract, Rosa Multiflora Flower Extract, Ethylhexylglycerin, Robinia Pseudoacacia Flower Extract, Potassium Hydroxide, Sodium Hyaluronate, Asiaticoside, Pulsatilla Koreana Extract, Zanthoxylum Piperitum Fruit Extract, Usnea Barbata (Lichen) Extract, Sh-Oligopeptide-1, Fragrance

PURPOSE

Skin Brightening
Anti wrinkle

WARNINGS

For external use only. Avoid contact with eyes. Do not use in areas with wounds. Keep out of reach of children. Discontinue use if signs of irritation appear. Store away from direct sunlight.

KEEP OUT OF REACH OF CHILDREN

Uses

■ Hydrogel facial mask
■ Helps brighten skin tone
■ Helps improve wrinkle problem
■ Strengthening the skin barrier
■ Enhance moisturizing function
■ Enhancement of antioxidant function

Directions

■ Gently prepare your face with toner after cleansing.
■ Remove the film on both sides of the mask gel sheet
■ Gently attach the transparent film side of the mask gel sheet to the skin surface
■ Remove the mask gel sheet after 20-30 minute and gently pat the remaining emulsion essence for absorption.
■ If necessary, cleanse the skin with water to cleanse the skin